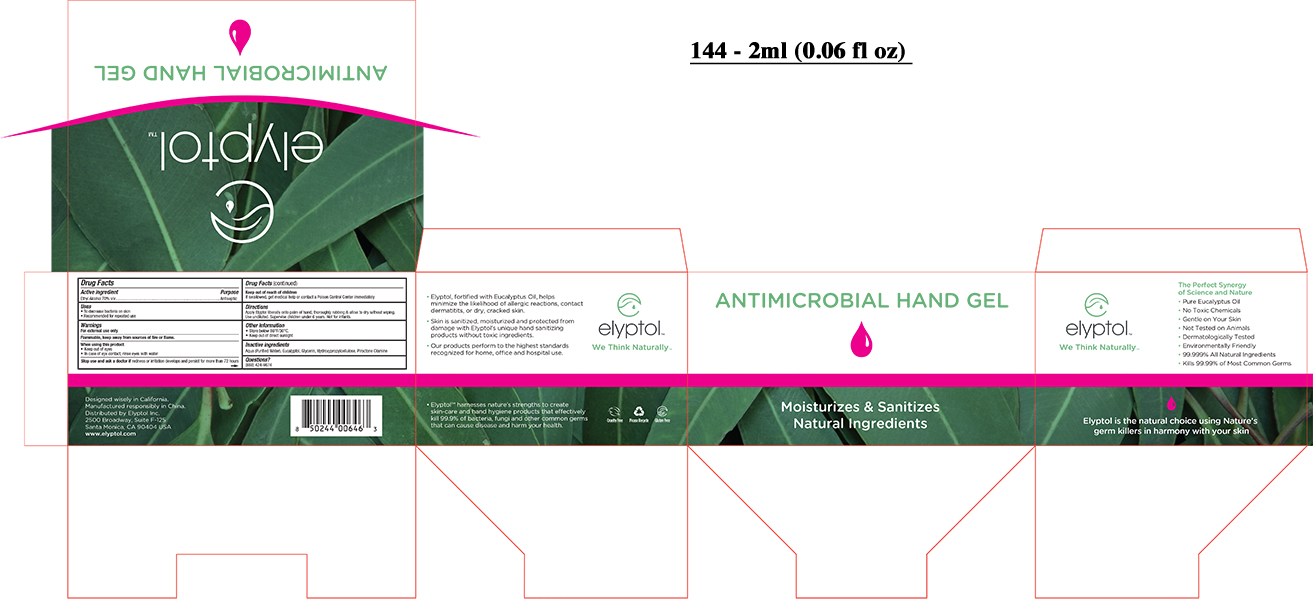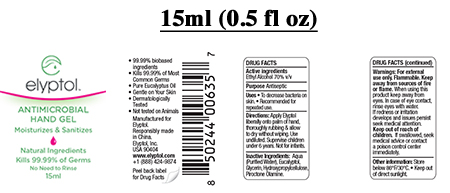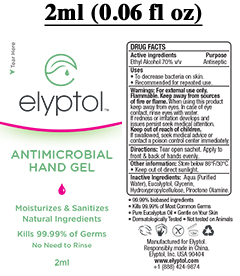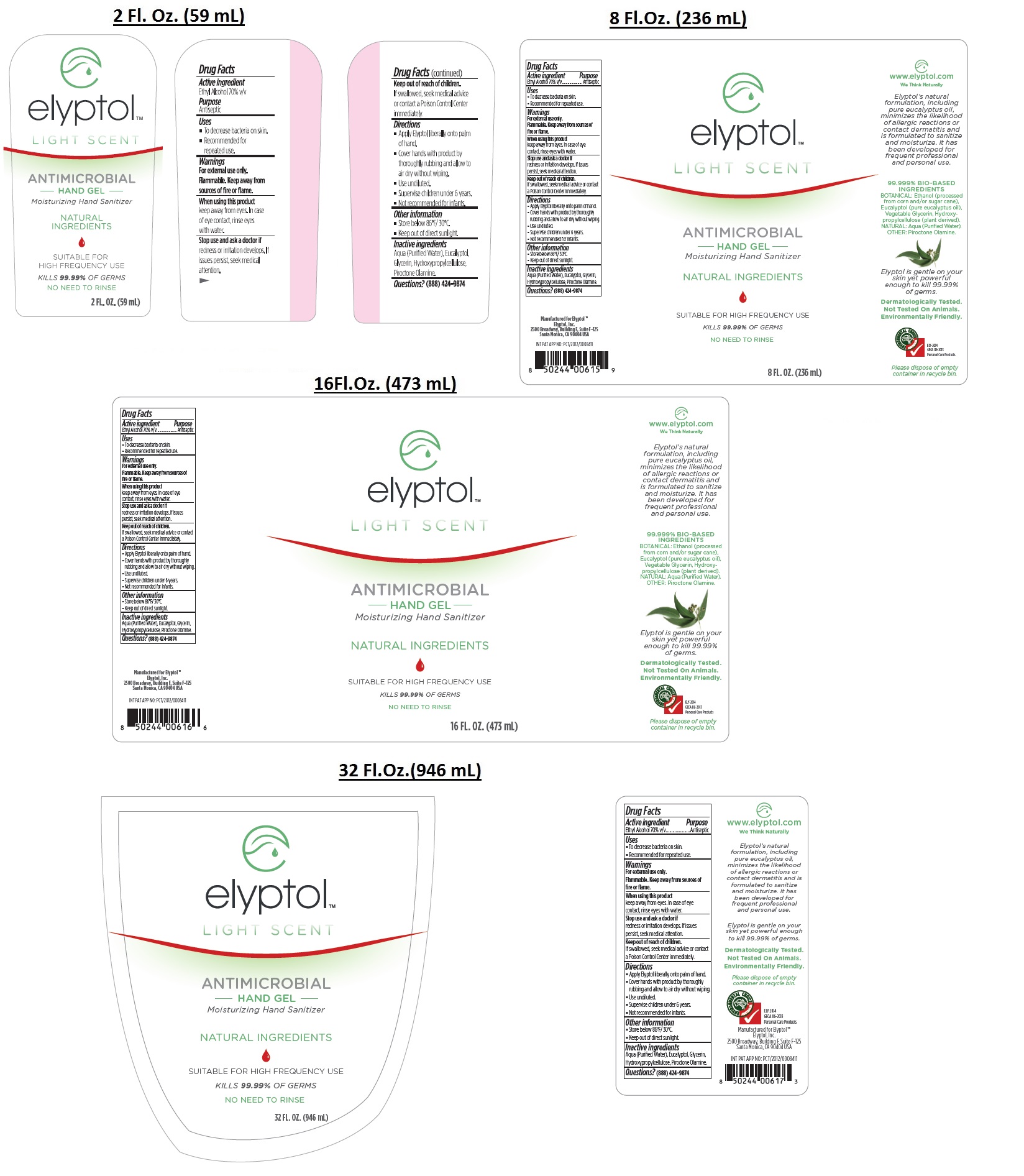 DRUG LABEL: Elyptol Light Scent- Antimicrobial Hand Gel
NDC: 69343-421 | Form: GEL
Manufacturer: ELYPTOL INC.
Category: otc | Type: HUMAN OTC DRUG LABEL
Date: 20221219

ACTIVE INGREDIENTS: ALCOHOL 7 mL/10 mL
INACTIVE INGREDIENTS: WATER; EUCALYPTOL; GLYCERIN; HYDROXYPROPYL CELLULOSE (1600000 WAMW); PIROCTONE OLAMINE

Elyptol Light Scent- Antimicrobial Hand Gel

Drug Facts

Active ingredient:

Ethyl Alcohol 70% v/v

Purpose

Antiseptic

Keep out reach of children

If swallowed, seek medical advice or contact a Poison Control Center immediately.

Uses

- To decrease bacteria on skin.
- Recommended for repeated use.

Warnings

For external use only
Flammable. Keep away from sources of fire or flame.

When using this product
keep away from eyes. In case of eye contact, rinse eyes with water.

Stop use and ask a doctor if
redness or irritation develops. If issues persist, seek medical attention.

Directions

- Apply Elyptol liberally onto palm of hand.
- Cover hands with product by thoroughly rubbing and allow to air dry without wiping
- Use undiluted
- Supervise children under 6 years
- Not recommended for infants

Other information

- Store below 86°F/30°C
- Keep out of direct sunlight.

Inactive ingredients

Aqua (Purified Water), Eucalyptol, Glycerin, Hydroxypropylcellulose, Piroctone Olamine.

Questions?(888) 424-9874

Moisturizing Hand Sanitizer

NATURAL INGREDIENTS

SUITABLE FOR HIGH FREQUENCY USE

KILLS 99.99% of GERMS

NO NEED TO RINSE

Dermatologically Tested

Not Tested On Animals